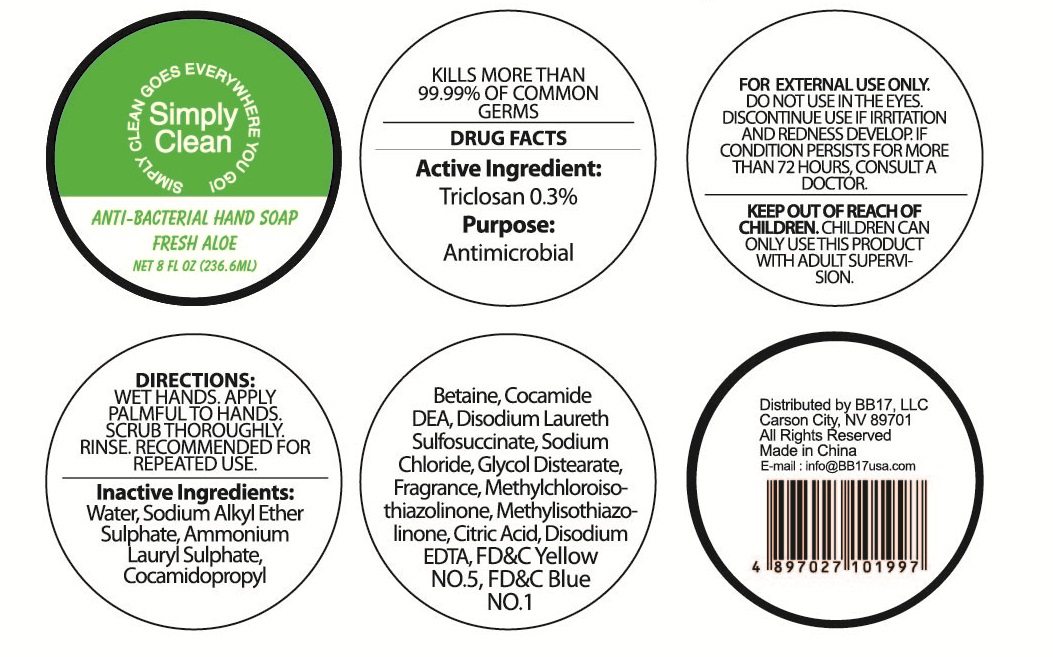 DRUG LABEL: Anti-bacterial Fresh Aloe Hand 
                
NDC: 53603-2015 | Form: SOAP
Manufacturer: BB17, LLC
Category: otc | Type: HUMAN OTC DRUG LABEL
Date: 20130820

ACTIVE INGREDIENTS: TRICLOSAN 0.3 g/100 mL
INACTIVE INGREDIENTS: WATER; SODIUM C12-15 PARETH-3 SULFATE; AMMONIUM LAURYL SULFATE; COCAMIDOPROPYL BETAINE; COCO DIETHANOLAMIDE; DISODIUM LAURETH SULFOSUCCINATE; SODIUM CHLORIDE; GLYCOL DISTEARATE; METHYLCHLOROISOTHIAZOLINONE; METHYLISOTHIAZOLINONE; CITRIC ACID MONOHYDRATE; EDETATE DISODIUM; FD&C YELLOW NO. 5; FD&C BLUE NO. 1

Active ingredient:

Triclosan 0.3%

Purpose
Antimicrobial

INDICATIONS AND USAGE

KILLS MORE THAN 99.99% OF COMMON GERMS

WARNINGS

FOR EXTERNAL USE ONLY.

DO NOT USE IN THE EYES.

DISCONTINUE USE IF IRRITATION AND REDNESS DEVELOP.

IF CONDITION PERSISTS FOR MORE THAN 72 HOURS, CONSULT A DOCTOR.

Keep out of reach of children.

CHILDREN CAN ONLY USE THIS PRODUCT WITH ADULT SUPERVISION.

DIRECTIONS:

WET HANDS.APPLY PALMFUL TO HANDS. SCRUB THOROUGHLY.

RINISE. RECOMMENDED FOR REPEATED USE.

INACTIVE INGREDIENT

INACTIVE INGREDIENTS:Water, Sodium Alkyl Ether Sulphate, Ammonium Lauryl Sulphate, Cocamidopropyl Betaine, Cocamide DEA, Disodium Laureth Sulfosuccinate, Sodium Chloride, Glycol Distearate, Fragrance, Methylchloroisothiazolinone, Methylisothiazolinone, Citric Acid, Disodium EDTA, FD&C Yellow NO. 5, FD&C Blue NO. 1